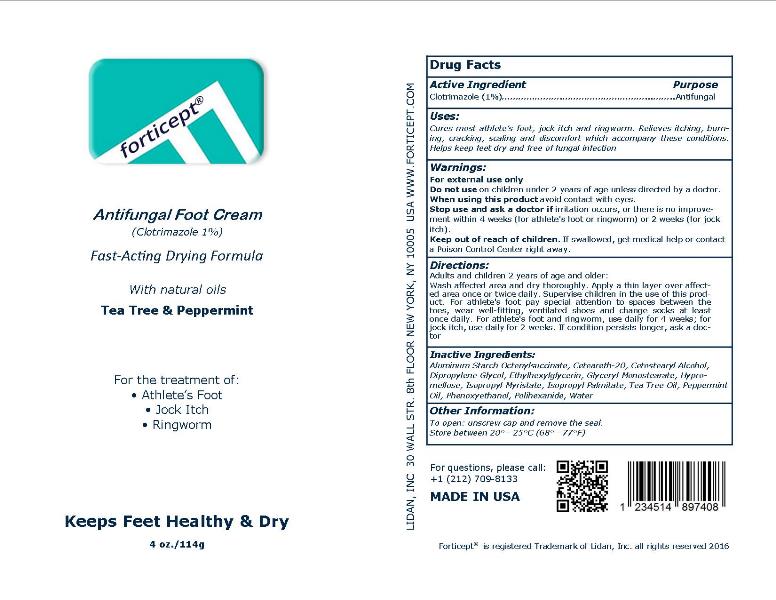 DRUG LABEL: Forticept Antifungal Foot Cream
NDC: 72127-0801 | Form: CREAM
Manufacturer: Lidan, Inc.
Category: otc | Type: HUMAN OTC DRUG LABEL
Date: 20250307

ACTIVE INGREDIENTS: CLOTRIMAZOLE 0.01 kg/1 kg
INACTIVE INGREDIENTS: ALUMINUM STARCH OCTENYLSUCCINATE; POLYOXYL 20 CETOSTEARYL ETHER; CETOSTEARYL ALCOHOL; DIPROPYLENE GLYCOL; ETHYLHEXYLGLYCERIN; GLYCERYL MONOSTEARATE; HYPROMELLOSE, UNSPECIFIED; ISOPROPYL MYRISTATE; ISOPROPYL PALMITATE; TEA TREE OIL; PEPPERMINT OIL; PHENOXYETHANOL; POLIHEXANIDE; WATER

Forticept Antifungal Foot Cream

DRUG FACTS

Active Ingredient/Purpose

Clotrimazole - 1% (Antifungal)

Uses

• Cures most athlete's foot, jock itch and ringworm
• Relieves itching, burning, cracking, scaling and discomfort which accompany these conditions
• Helps keep feet dry and free of fungal infection

INDICATIONS AND USAGE

For the treatment of fungal infections caused by: Athlete's foot (tinea pedis), Jock itch (tinea cruris), and Ringworm (tinea corporis)

WARNINGS:

For external use only!

Keep out of reach of children. If swallowed, get medical help or contact a Poison Control Center right away

Do not use on children under 2 years of age unless directed by a doctor.

Stop use and ask a doctor if:
• irritation occurs
• there is no improvement within 4 weeks (for athlete's foot or ringworm) or 2 weeks (for jock itch).

When using this product avoid contact with eyes.

DIRECTIONS:

Adults and children 2 years of age and older:
• wash affected area and dry thoroughly
• apply a thin layer over affected area once or twice daily
• supervise children in the use of this product
• for athlete's foot, pay special attention to spaces between the toes, wear well-fitting, ventilated
• shoes and change socks at least once daily
• for athlete's foot and ringworm, use daily for 4 weeks; for jock itch, use daily for 2 weeks
• if condition persists longer, ask a doctor

Inactive Ingredients:

ALUMINUM STARCH OCTENYLSUCCINATE, CETEARETH-20, CETOSTEARYL ALCOHOL, DIPROPYLENE GLYCOL, ETHYLHEXYLGLYCERIN, GLYCERYL MONOSTEARATE, HYPROMELLOSE, ISOPROPYL MYRISTATE, ISOPROPYL PALMITATE, TEA TREE OIL, PEPPERMINT OIL, PHENOXYETHANOL, POLIHEXANIDE, WATER

Other Information:

• To open: unscrew cap and remove the seal.
• Store between 68° - 77°F (20° - 25°C)

For Questions:

Please call: +1 212 709-8133
Lidan, Inc.
30 Wall Street, 8th Floor
New York, NY 10005
www.forticept.com